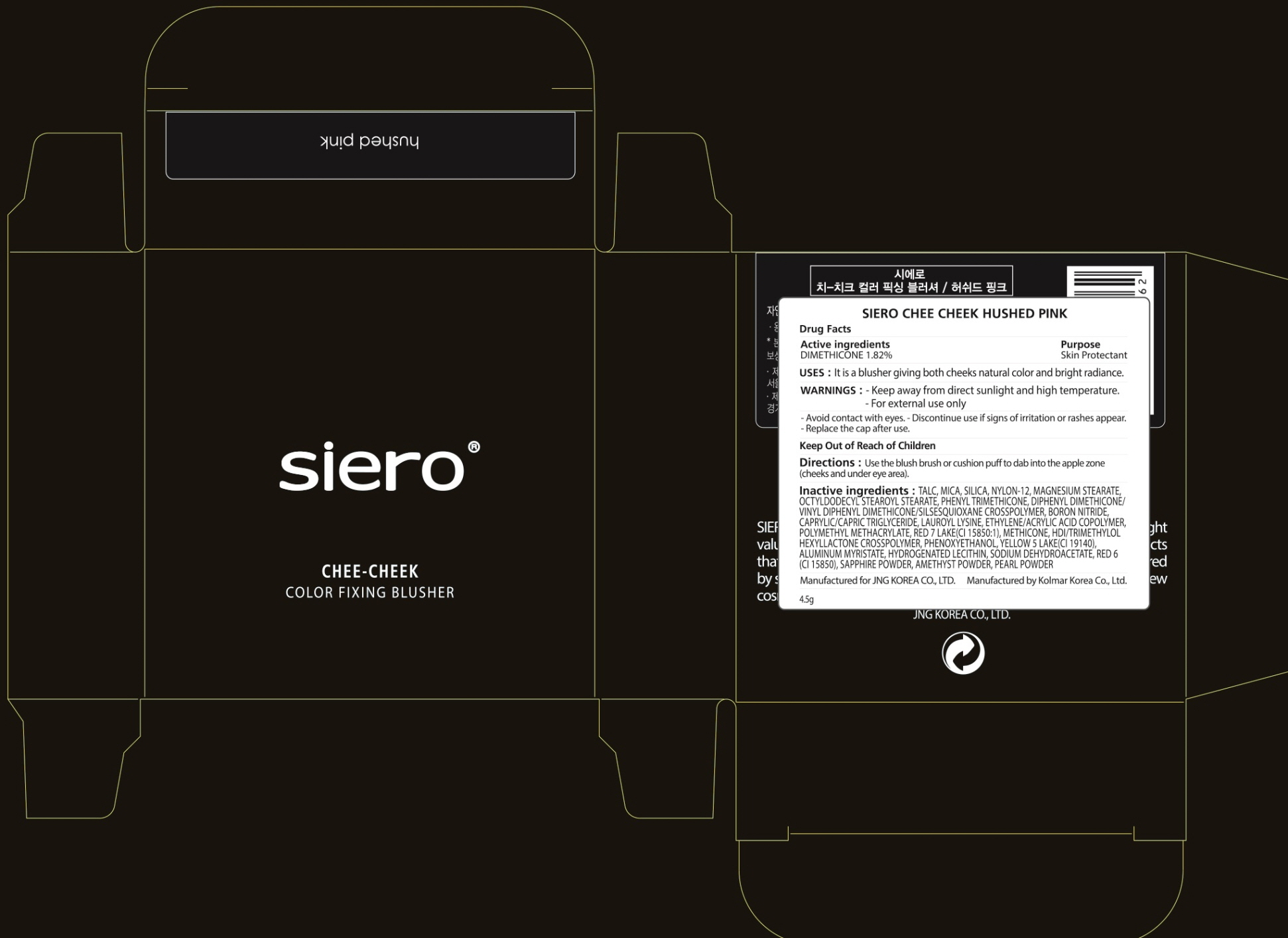 DRUG LABEL: SIERO CHEE CHEEK HUSHED PINK
NDC: 71472-230 | Form: POWDER
Manufacturer: JNG KOREA CO.,LTD.
Category: otc | Type: HUMAN OTC DRUG LABEL
Date: 20170630

ACTIVE INGREDIENTS: DIMETHICONE 0.08 g/4.5 g
INACTIVE INGREDIENTS: TALC; MICA

ACTIVE INGREDIENT

Active ingredients: DIMETHICONE 1.82%

INACTIVE INGREDIENT

Inactive ingredients: TALC, MICA, SILICA, NYLON-12, MAGNESIUM STEARATE, OCTYLDODECYL STEAROYL STEARATE, PHENYL TRIMETHICONE, DIPHENYL DIMETHICONE/VINYL DIPHENYL DIMETHICONE/SILSESQUIOXANE CROSSPOLYMER, BORON NITRIDE, CAPRYLIC/CAPRIC TRIGLYCERIDE, LAUROYL LYSINE, ETHYLENE/ACRYLIC ACID COPOLYMER, POLYMETHYL METHACRYLATE, RED 7 LAKE(CI 15850:1), METHICONE, HDI/TRIMETHYLOL HEXYLLACTONE CROSSPOLYMER, PHENOXYETHANOL, YELLOW 5 LAKE(CI 19140), ALUMINUM MYRISTATE, HYDROGENATED LECITHIN, SODIUM DEHYDROACETATE, RED 6 (CI 15850), SAPPHIRE POWDER, AMETHYST POWDER, PEARL POWDER

PURPOSE

Purpose: Skin Protectant

WARNINGS

Warnings: - Keep away from direct sunlight and high temperature. - For external use only Avoid contact with eyes. Discontinue use if signs of irritation or rashes appear. Replace the cap after use.

KEEP OUT OF REACH OF CHILDREN

Uses

Uses: It is a blusher giving both cheeks natural color and bright radiance.

Directions

Directions: Use the blush brush or cushion puff to dab into the apple zone (cheeks and under eye area).